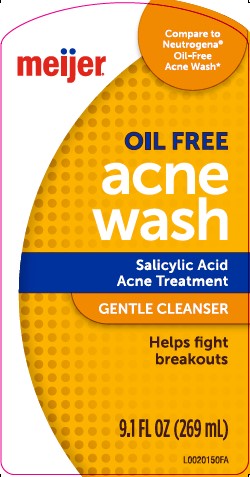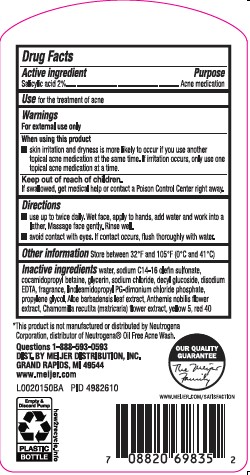 DRUG LABEL: Oil Free Acne Wash
NDC: 41250-947 | Form: LOTION
Manufacturer: Meijer, Inc.
Category: otc | Type: HUMAN OTC DRUG LABEL
Date: 20260224

ACTIVE INGREDIENTS: SALICYLIC ACID 20.6 mg/1 mL
INACTIVE INGREDIENTS: WATER; SODIUM C14-16 OLEFIN SULFONATE; COCAMIDOPROPYL BETAINE; GLYCERIN; SODIUM CHLORIDE; DECYL GLUCOSIDE; EDETATE DISODIUM ANHYDROUS; LINOLEAMIDOPROPYL PG-DIMONIUM CHLORIDE PHOSPHATE; PROPYLENE GLYCOL; ALOE VERA LEAF; CHAMAEMELUM NOBILE FLOWER; CHAMOMILE; FD&C YELLOW NO. 5; FD&C RED NO. 40

Meijer 947.003/947AC-AD
Oil-Free Acne Wash

Active ingredient

Salicylic acid 2%

Purpose

Acne medication

Use

for the treatment of acne

Warnings

For external use only

When using this product

- skin irritation and dryness is more likely to occur if you use another topical acne medication at the same time. If irritation occurs, only use one topical acne medication at a time

Keep out of reach of children.

If swallowed, get medical help or contact a Poison Control Center right away.

Directions

- use twice a daily. Wet face, apply to hands, add water and work into lather. Massage face gently. Rinse well.
- avoid contact with eyes. If contact occurs, flush thoroughly with water.

Other information

Store between 32ºF and 105F (0C and 41C)

Inactive ingredients

water, sodium C14-16 olefin sulfonate, cocamidopropyl betaine, glycerin, sodium chloride, decyl glucoside, disodium EDTA, fragrance, linoleamidopropyl PG-dimonium chloride phosphate, propylene glycol, Aloe barbadensis leaf extract, Anthemis nobilis flower extract, Chamomilla recutita (matricaria) flower extract, yellow 5, red 40

Disclaimer

*This product is not manufactured or distributed by Neutrogena Corporation, distributor of NeutrogenaOil Free Acne Wash.

ADVERSE REACTION

Questions 1-888-593-0593

DIST. BY MEIJER DISTRIBUTION, INC

GRAND RAPIDS, MI 49544

www.meijer.com

OUR QUALITY GUARANTEE

The Meijer Family

www.meijer.com/satisfaction

Empty & Discard Pump

PLASTIC BOTTLE

how2recycle.info

principal display panel

meijer®

Compare to Neutrogena®Oil-Free Acne Wash*

OIL FREE

ACNE WASH

Salicylic Acid

Acne Treatment

GENTLE CLEANSER

Helps fight breakouts

9.1 FL OZ (269 mL)